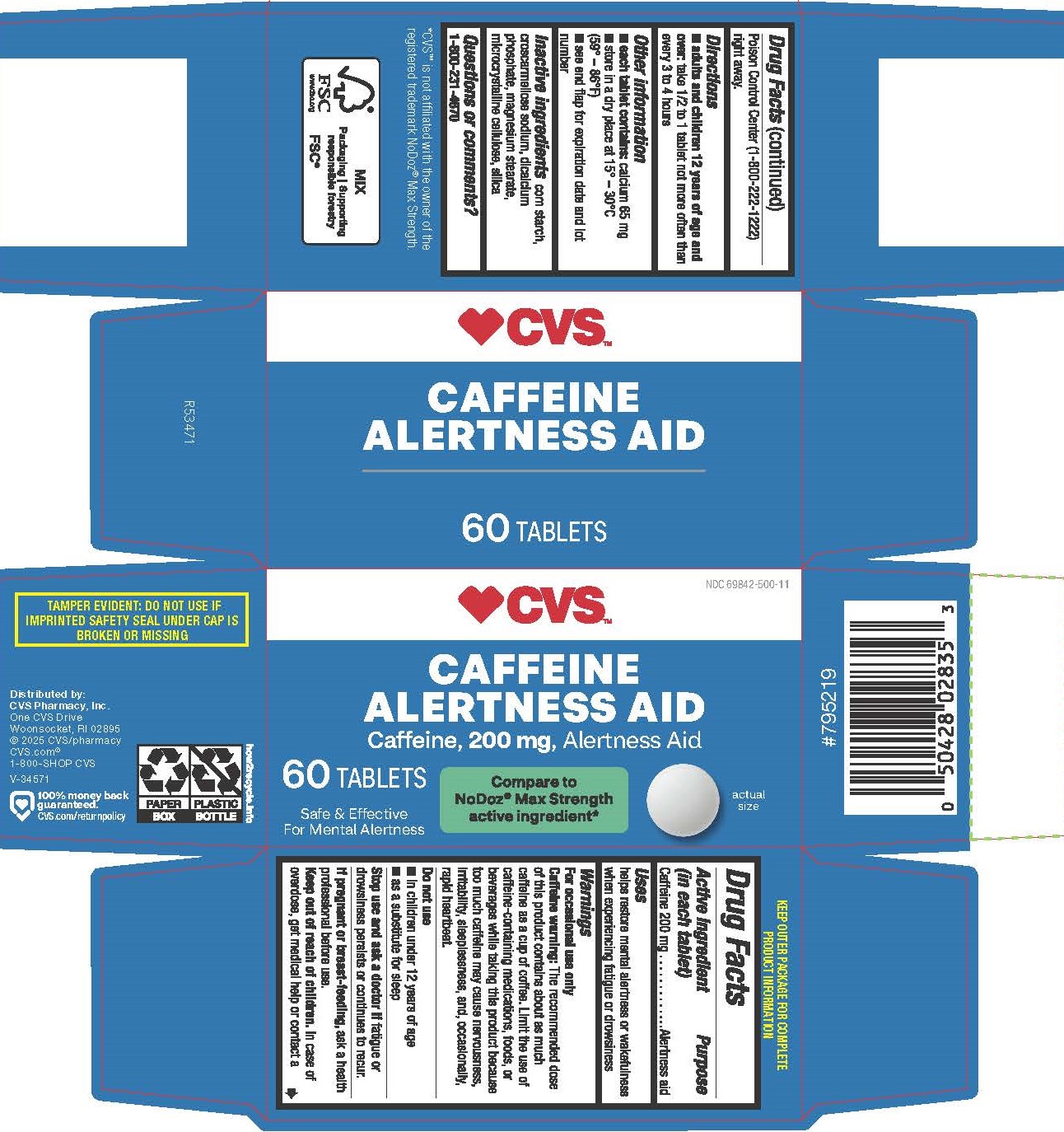 DRUG LABEL: Caffeine
NDC: 69842-500 | Form: TABLET
Manufacturer: CVS Pharmacy, Inc.
Category: otc | Type: HUMAN OTC DRUG LABEL
Date: 20251016

ACTIVE INGREDIENTS: CAFFEINE 200 mg/1 1
INACTIVE INGREDIENTS: CROSCARMELLOSE SODIUM; STARCH, PREGELATINIZED CORN; CALCIUM PHOSPHATE, DIBASIC, DIHYDRATE; MICROCRYSTALLINE CELLULOSE; SILICON DIOXIDE; MAGNESIUM STEARATE

5350-CVS

Drug Facts

Active ingredient (in each tablet)

Caffeine 200 mg

Purpose

Alertness aid

Uses

helps restore mental alertness or wakefulness when experiencing fatigue or drowsiness

WARNINGS

For occasional use only

Caffeine warning: The recommended dose of this product contains about as much caffeine as a cup of coffee. Limit

the use of caffeine-containing medications, foods, or beverages while taking this product because too much caffeine may cause

nervousness, irritability, sleeplessness, and, occasionally, rapid heartbeat.

Do not use

■ in children under 12 years of age

■ as a substitute for sleep

Stop use and ask a doctor if fatigue or drowsiness persists or continues to recur.

PREGNANCY OR BREAST FEEDING

If pregnant or breast-feeding, ask a health professional before use

Keep out of reach of children.

OVERDOSAGE

In case of overdose, get medical help or contact a Poison Control Center (1-800-222-1222) right away.

Directions

■ adults and children 12 years of age and over: take 1/2 to 1 tablet not more often than every 3 to 4 hours

Other Information

■ each tablet contains: calcium 65 mg

■ store in a dry place at 15°-30°C (59°-86°F)

■ see end flap for expiration date and lot number

INACTIVE INGREDIENT

corn starch, croscarmellose sodium, dicalcium phosphate, magnesium stearate, microcrystalline cellulose, silica

Questions or comments?

1-800-231-4670

TAMPER EVIDENT: DO NOT USE IF IMPRINTED SAFETY SEAL UNDER CAP IS BROKEN OR MISSING

KEEP OUTER PACKAGE FOR COMPLETE PRODUCT INFORMATION

*CVS™ is not affiliated with the owner of the registered trademark NoDoz® Max Strength.

Distributed by: CVS Pharmacy, Inc.

One CVS Drive, Woonsocket, RI 02895

© 2025 CVS/pharmacy

CVS.com® 1-800-SHOP CVS V-34571

PACKAGE LABEL

CVS™

NDC 69842-500-11

CAFFEINE

ALERTNESS AID

Caffeine, 200 mg, Alertness Aid

Compare to NoDoz® Max Strength active ingredient*

60 TABLETS

Safe & Effective

For Mental Alertness